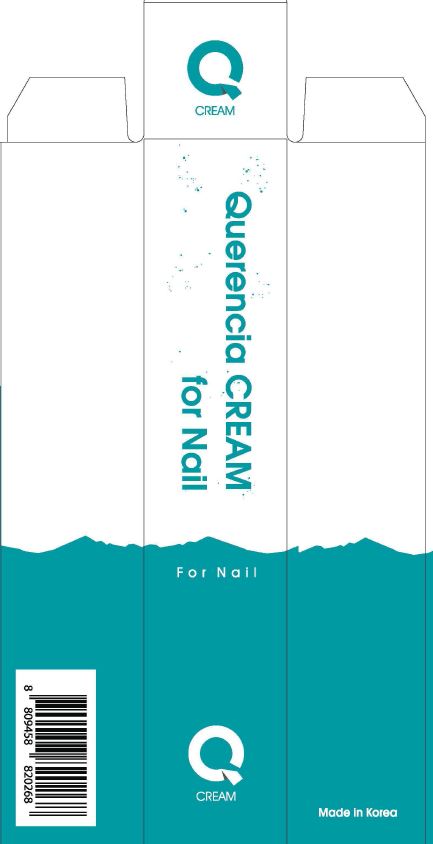 DRUG LABEL: Querencia CREAMfor Skin
NDC: 70488-0008 | Form: LIQUID
Manufacturer: MUSEE Cosmetic Co.,Ltd.
Category: otc | Type: HUMAN OTC DRUG LABEL
Date: 20190104

ACTIVE INGREDIENTS: DIMETHICONE 8 g/100 mL
INACTIVE INGREDIENTS: WATER; BUTYLENE GLYCOL

Drug Facts

ACTIVE INGREDIENT

dimethicone

INACTIVE INGREDIENT

Water, Butylene Glycol, Bentonite, SparassisCrispa Extract, Betaine, Methyl Gluceth-20, Isononyl Isononanoate, Cyclopentasiloxane, Glycerin, Niacinamide, Hydrogenated Poly(C6-14 Olefin), Caprylic/Capric Triglyceride, Cyclohexasiloxane, Cetearyl Alcohol, Boswellia Serrata Extract, CentellaAsiatica Extract, Dioscorea Japonica Root Extract, Portulaca Oleracea Extract, Caprylyl Glycol, Dimethicone/Vinyl DimethiconeCrosspolymer, 1,2-Hexanediol, Sodium Polyacrylate, Acrylates/C10-30 Alkyl Acrylate Crosspolymer, Tocopheryl Acetate, Tromethamine, Carbomer, Sodium Hyaluronate, Dipotassium Glycyrrhizate, Ethylhexylglycerin, Adenosine, Hydrolyzed Corn Starch, XANTHAN GUM, Disodium EDTA, Trideceth-6, PEG/PPG-18/18 Dimethicone, Beta-Glucan, Sucrose, PEG-100 Stearate, Glyceryl Stearate, Cetearyl Glucoside, SorbitanOlivate, SorbitanSesquioleate, Polysorbate 60, Stearic Acid, Fragrance

PURPOSE

Problematic nails and skin improvement moisturizer

keep out of reach of the children

INDICATIONS AND USAGE

Apply to the skin and gently rub it to absorb it

WARNINGS

1. Do not use in the following cases(Eczema and scalp wounds)
2.Side Effects
1)Due to the use of this druf if rash, irritation, itching and symptopms of hypersnesitivity occur dicontinue use and consult your phamacisr or doctor
3.General Precautions
1)If in contact with the eyes, wash out thoroughty with water If the symptoms are servere, seek medical advice immediately
2)This product is for exeternal use only. Do not use for internal use
4.Storage and handling precautions
1)If possible, avoid direct sunlight and store in cool and area of low humidity
2)In order to maintain the quality of the product and avoid misuse
3)Avoid placing the product near fire and store out in reach of children

DOSAGE AND ADMINISTRATION

for topical use only